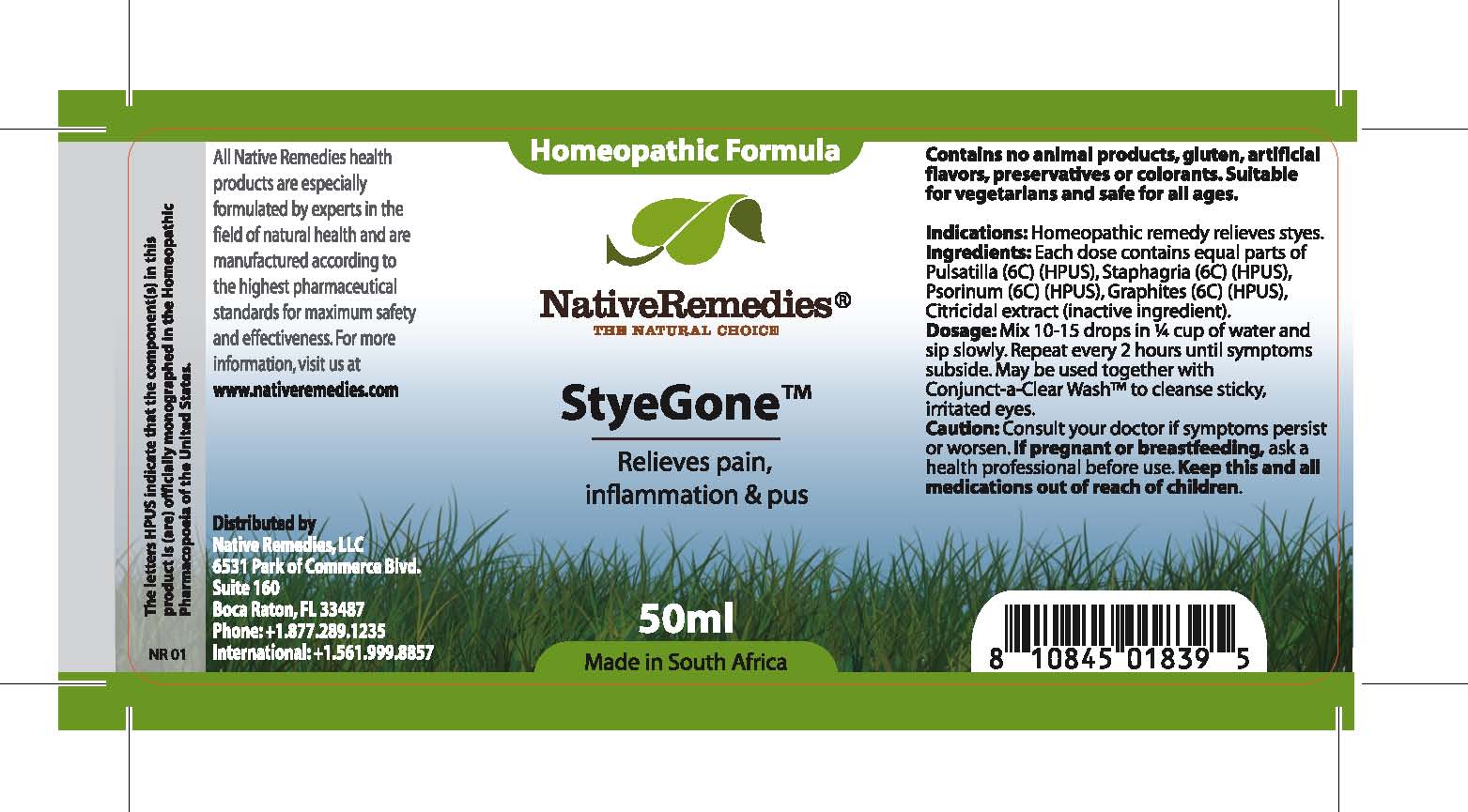 DRUG LABEL: StyeGone
NDC: 68647-195 | Form: TINCTURE
Manufacturer: Feelgood Health
Category: homeopathic | Type: HUMAN OTC DRUG LABEL
Date: 20100817

ACTIVE INGREDIENTS: PULSATILLA PATENS 6 [hp_C]/50 mL; DELPHINIUM STAPHISAGRIA SEED 6 [hp_C]/50 mL; SCABIES LESION LYSATE (HUMAN) 6 [hp_C]/50 mL; GRAPHITE 6 [hp_C]/50 mL
INACTIVE INGREDIENTS: CITRUS PARADISI SEED 0.03 mL/50 mL; WATER 98.97 mL/50 mL

STYEGONE

PURPOSE

Relieves pain, inflammation and pus

Indications: Homeopathic remedy relieves styes.

DOSAGE AND ADMINISTRATION

Dosage: Mix 10-15 drops in ¼ cup of water and sip slowly. Repeat every 2 hours until symptoms subside. May be used together with Conjunct-a-Clear Wash™ to cleanse sticky, irritated eyes.

GENERAL PRECAUTIONS

Caution: Consult your doctor if symptoms persist or worsen. Keep this and all medications out of reach of children.

ACTIVE INGREDIENT

Ingredients: Each dose contains equal parts of Pulsatilla (6C) (HPUS), Staphagria (6C) (HPUS), Psorinum (6C) (HPUS), Graphites (6C) (HPUS)

Citricidal extract (inactive ingredient).

PREGNANCY

If pregnant or breastfeeding, ask a health professional before use.

WARNINGS

Contains no animal products, gluten, artificial flavors, preservatives or colorants. Suitable for vegetarians and safe for all ages.

PATIENT COUNSELING INFORMATION

All Native Remedies health products are especially formulated by experts in the field of natural health and are manufactured according to the highest pharmaceutical standards for maximum safety and effectiveness. For more information, visit us at www.nativeremedies.com

Distributed by

Native Remedies, LLC

6531 Park of Commerce Blvd.

Suite 160

Boca Raton, FL 33487

Phone: 1.877.289.1235

International: + 1.561.999.8857

The letters HPUS indicate that the component(s) in this product is (are) officially monographed in the Homeopathic Pharmacopoeia of the United States.

KEEP OUT OF REACH OF CHILDREN

Keep this and all medications out of reach of children.